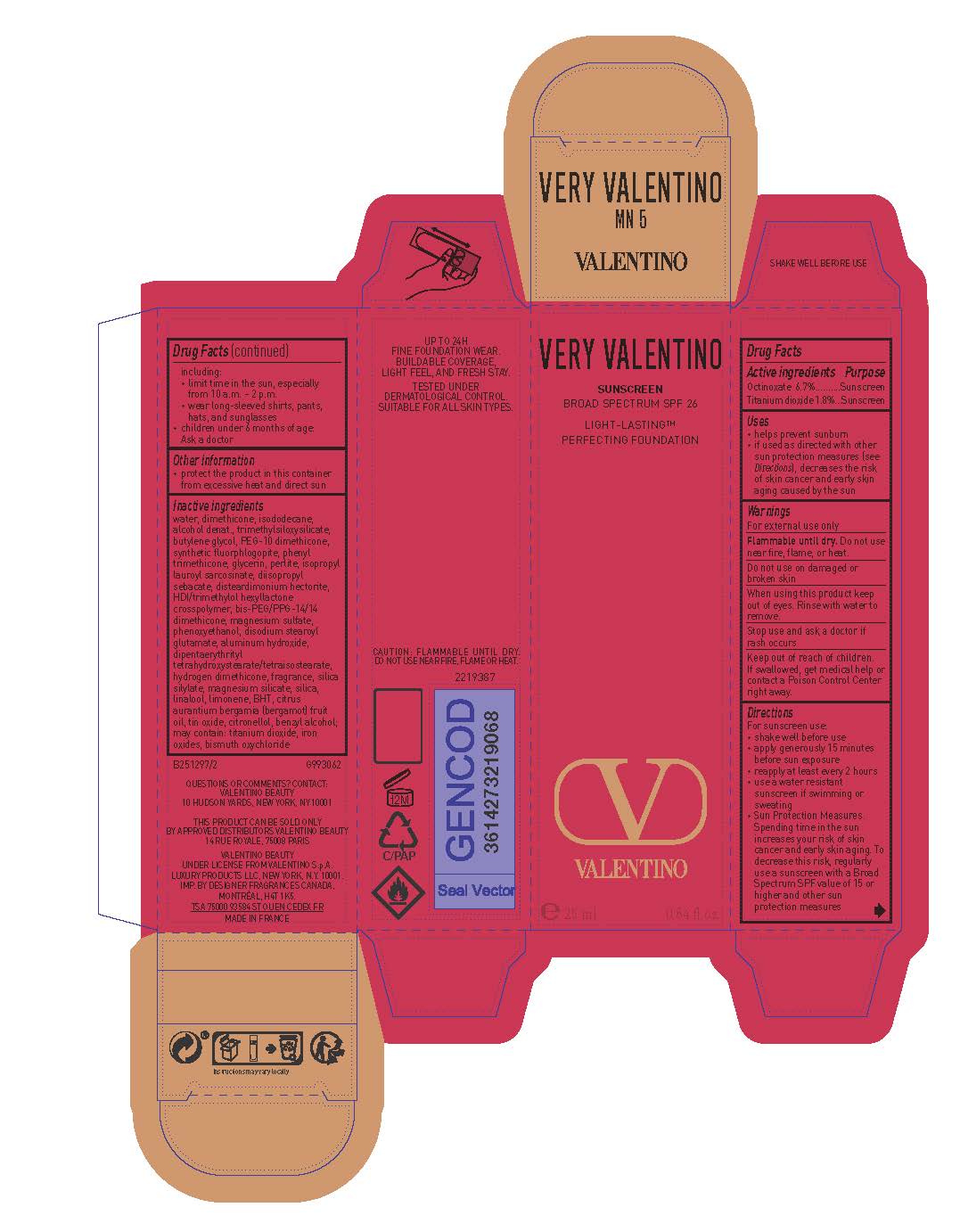 DRUG LABEL: Valentino Very Valentino Light Lasting Perfecting Foundation Broad Spectrum SPF 26 Sunscreen
NDC: 51150-180 | Form: LOTION
Manufacturer: SICOS ET CIE
Category: otc | Type: HUMAN OTC DRUG LABEL
Date: 20231218

ACTIVE INGREDIENTS: OCTINOXATE 67 mg/1 mL; TITANIUM DIOXIDE 18 mg/1 mL
INACTIVE INGREDIENTS: WATER; DIMETHICONE; ISODODECANE; ALCOHOL; TRIMETHYLSILOXYSILICATE (M/Q 0.8-1.0); BUTYLENE GLYCOL; PEG-10 DIMETHICONE (600 CST); MAGNESIUM POTASSIUM ALUMINOSILICATE FLUORIDE; PHENYL TRIMETHICONE; GLYCERIN; PERLITE; ISOPROPYL LAUROYL SARCOSINATE; DIISOPROPYL SEBACATE; DISTEARDIMONIUM HECTORITE; HEXAMETHYLENE DIISOCYANATE/TRIMETHYLOL HEXYLLACTONE CROSSPOLYMER; BIS-PEG/PPG-14/14 DIMETHICONE; MAGNESIUM SULFATE, UNSPECIFIED FORM; PHENOXYETHANOL; DISODIUM STEAROYL GLUTAMATE; ALUMINUM HYDROXIDE; DIPENTAERYTHRITYL TETRAHYDROXYSTEARATE/TETRAISOSTEARATE; HYDROGEN DIMETHICONE (13 CST); MAGNESIUM SILICATE; SILICON DIOXIDE; LINALOOL, (+/-)-; LIMONENE, (+)-; BUTYLATED HYDROXYTOLUENE; BERGAMOT OIL; STANNIC OXIDE; .BETA.-CITRONELLOL, (R)-; BENZYL ALCOHOL; FERRIC OXIDE RED; BISMUTH OXYCHLORIDE

Drug Facts

Active ingredients

Octinoxate 6.7%

Titanium dioxide 1.8%

Purpose

Sunscreen

Uses

- helps prevent sunburn
- if used as directed with other sun protection measures (see Directions), decreases the risk of skin cancer and early skin aging caused by the sun

Warnings

For external use only

Flammable until dry.

Do not use near fire, flame or heat.

Do not use

on damaged or broken skin

When using this product

keep out of eyes. Rinse with water to remove.

Stop use and ask a doctor if

rash occurs

Keep out of reach of children.

If swallowed, get medical help or contact a Poison Control Center right away.

Directions

For sunscreen use:

● shake well before use

● apply generously 15 minutes before sun exposure

● reapply at least every 2 hours

● use a water resistant sunscreen if swimming or sweating

● Sun Protection Measures. Spending time in the sun increases your risk of skin cancer and early skin aging. To decrease this risk, regularly use a sunscreen with a Broad Spectrum SPF value of 15 or higher and other sun protection measures including:

● limit time in the sun, especially from 10 a.m. – 2 p.m.

● wear long-sleeved shirts, pants, hats, and sunglasses

● children under 6 months of age: Ask a doctor

Other information

protect the product in this container from excessive heat and direct sun

Inactive ingredients

water, dimethicone, isododecane, alcohol denat., trimethylsiloxysilicate, butylene glycol,, PEG-10 dimethicone, synthetic fluorphlogopite, phenyl trimethicone, glycerin, perlite, isopropyl lauroyl sarcosinate, diisopropyl sebacate, disteardimonium hectorite, HDI/trimethylol hexyllactone crosspolymer, bis-PEG/PPG-14/14 dimethicone, magnesium sulfate, phenoxyethanol, disodium stearoyl glutamate, aluminum hydroxide, dipentaerythrityl tetrahydroxystearate/tetraisostearate, hydrogen dimethicone, fragrance, silica silylate, magnesium silicate, silica, linalool, limonene, BHT, citrus aurantium bergamia (bergamot) fruit oil, tin oxide, citronellol, benzyl alcohol; may contain: titanium dioxide, iron oxides, bismuth oxychloride